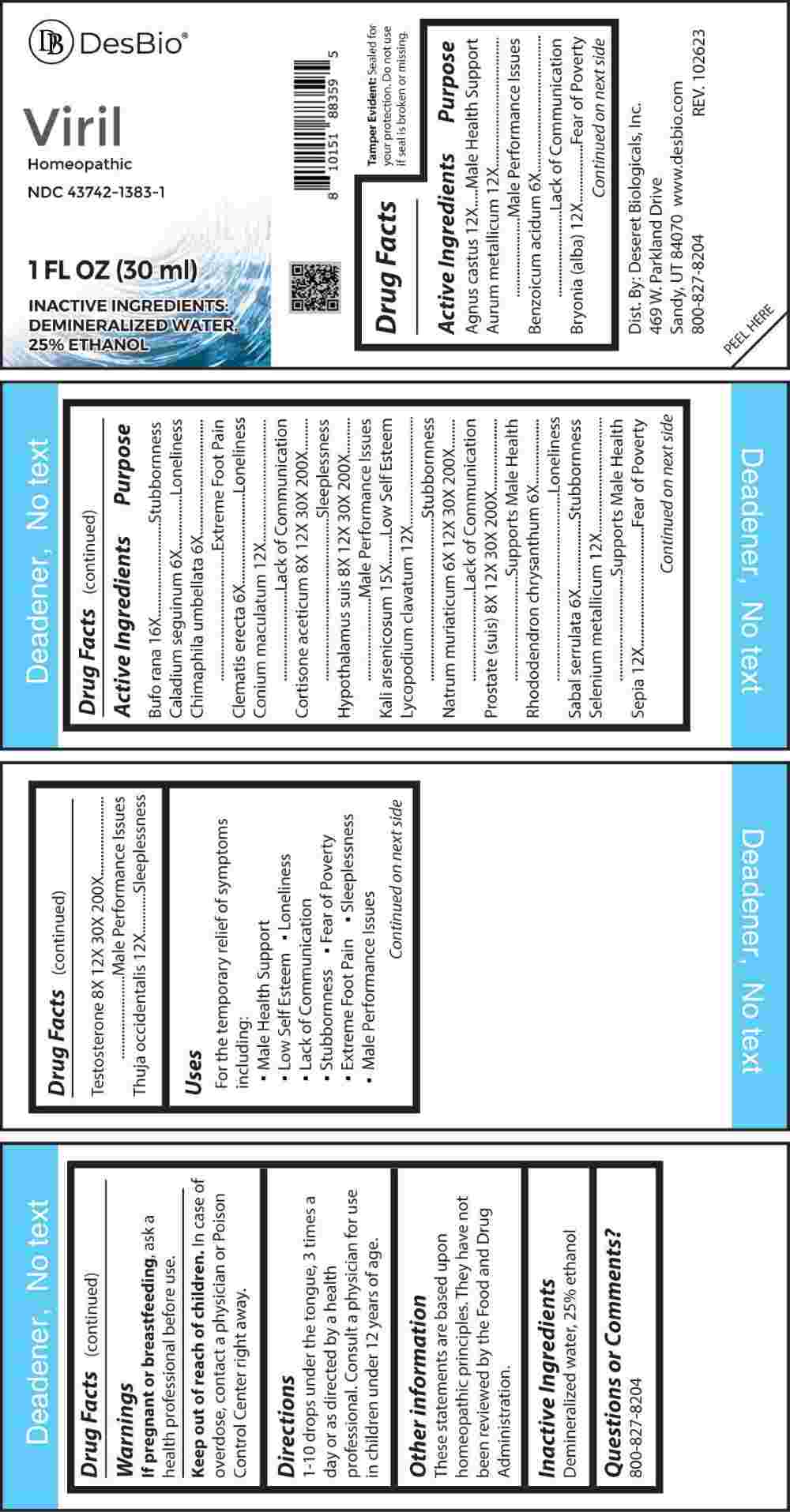 DRUG LABEL: Viril
NDC: 43742-1383 | Form: LIQUID
Manufacturer: Deseret Biologicals, Inc.
Category: homeopathic | Type: HUMAN OTC DRUG LABEL
Date: 20240312
DEA Schedule: CIII

ACTIVE INGREDIENTS: BENZOIC ACID 6 [hp_X]/1 mL; DIEFFENBACHIA SEGUINE 6 [hp_X]/1 mL; CHIMAPHILA UMBELLATA 6 [hp_X]/1 mL; CLEMATIS RECTA FLOWERING TOP 6 [hp_X]/1 mL; RHODODENDRON AUREUM LEAF 6 [hp_X]/1 mL; SAW PALMETTO 6 [hp_X]/1 mL; SODIUM CHLORIDE 6 [hp_X]/1 mL; CORTISONE ACETATE 8 [hp_X]/1 mL; SUS SCROFA HYPOTHALAMUS 8 [hp_X]/1 mL; SUS SCROFA PROSTATE 8 [hp_X]/1 mL; TESTOSTERONE 8 [hp_X]/1 mL; CHASTE TREE 12 [hp_X]/1 mL; GOLD 12 [hp_X]/1 mL; BRYONIA ALBA ROOT 12 [hp_X]/1 mL; CONIUM MACULATUM FLOWERING TOP 12 [hp_X]/1 mL; LYCOPODIUM CLAVATUM SPORE 12 [hp_X]/1 mL; SELENIUM 12 [hp_X]/1 mL; SEPIA OFFICINALIS JUICE 12 [hp_X]/1 mL; THUJA OCCIDENTALIS LEAFY TWIG 12 [hp_X]/1 mL; POTASSIUM ARSENITE ANHYDROUS 15 [hp_X]/1 mL; BUFO BUFO CUTANEOUS GLAND 16 [hp_X]/1 mL
INACTIVE INGREDIENTS: WATER; ALCOHOL

DRUG FACTS:

ACTIVE INGREDIENTS:

Agnus Castus 12X, Aurum Metallicum 12X, Benzoicum Acidum 6X, Bryonia (Alba) 12X, Bufo Rana 16X, Caladium Seguinum 6X, Chimaphila Umbellata 6X, Clematis Erecta 6X, Conium Maculatum 12X, Cortisone Aceticum 8X, 12X, 30X, 200X, Hypothalamus Suis 8X, 12X, 30X, 200X, Kali Arsenicosum 15X, Lycopodium Clavatum 12X, Natrum Muriaticum 6X, 12X, 30X, 200X, Prostate (Suis) 8X, 12X, 30X, 200X), Rhododendron Chrysanthum 6X, Sabal Serrulata 6X, Selenium Metallicum 12X, Sepia 12X, Testosterone 8X, 12X, 30X, 200X, Thuja Occidentalis 12X.

PURPOSE:

Agnus Castus – Male Health Support, Aurum Metallicum – Male Performance Issues, Benzoicum Acidum – Lack of Communication, Bryonia (Alba) – Fear of Poverty, Bufo Rana - Stubbornness, Caladium Seguinum - Loneliness, Chimaphila Umbellata – Extreme Foot Pain, Clematis Erecta - Loneliness, Conium Maculatum – Lack of Communication, Cortisone Aceticum - Sleeplessness, Hypothalamus Suis – Male Performance Issues, Kali Arsenicosum – Low Self Esteem, Lycopodium Clavatum - Stubbornness, Natrum Muriaticum – Lack of Communication, Prostate (Suis) – Supports Male Health, Rhododendron Chrysanthum - Loneliness, Sabal Serrulata - Stubbornness, Selenium Metallicum – Supports Male Health, Sepia – Fear of Poverty, Testosterone – Male Performance Issues, Thuja Occidentalis - Sleeplessness

USES:

For the temporary relief of symptoms including:

• Male Health Support • Low Self Esteem • Loneliness

• Lack of Communication • Stubbornness • Fear of Poverty

• Extreme Foot Pain • Sleeplessness • Male Performance Issues

These statements are based upon homeopathic principles. They have not been reviewed by the Food and Drug Administration.

WARNINGS:

If pregnant or breast-feeding, ask a health professional before use.

Keep out of reach of children. In case of overdose, contact a physician or Poison Control Center right away.

Tamper Evident: Sealed for your protection. Do not use if seal is broken or missing.

KEEP OUT OF REACH OF CHILDREN:

In case of overdose, contact a physician or Poison Control Center right away.

DIRECTIONS:

1-10 drops under the tongue, 3 times a day or as directed by a health professional. Consult a physician for use in children under 12 years of age.

INACTIVE INGREDIENTS:

Demineralized water, 25% ethanol

QUESTIONS:

Dist. By: Deseret Biologicals, Inc.
469 W. Parkland Drive
Sandy, UT 84070

www.desbio.com

800-827-8204

PACKAGE LABEL DISPLAY:

Des Bio

Viril

Homeopathic
NDC 43742-1383-1
1 FL OZ (30 ml)